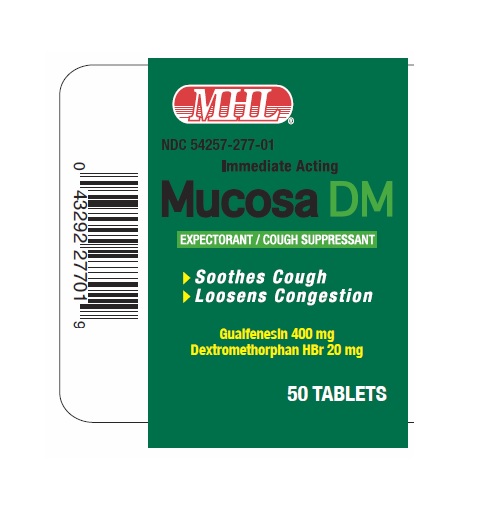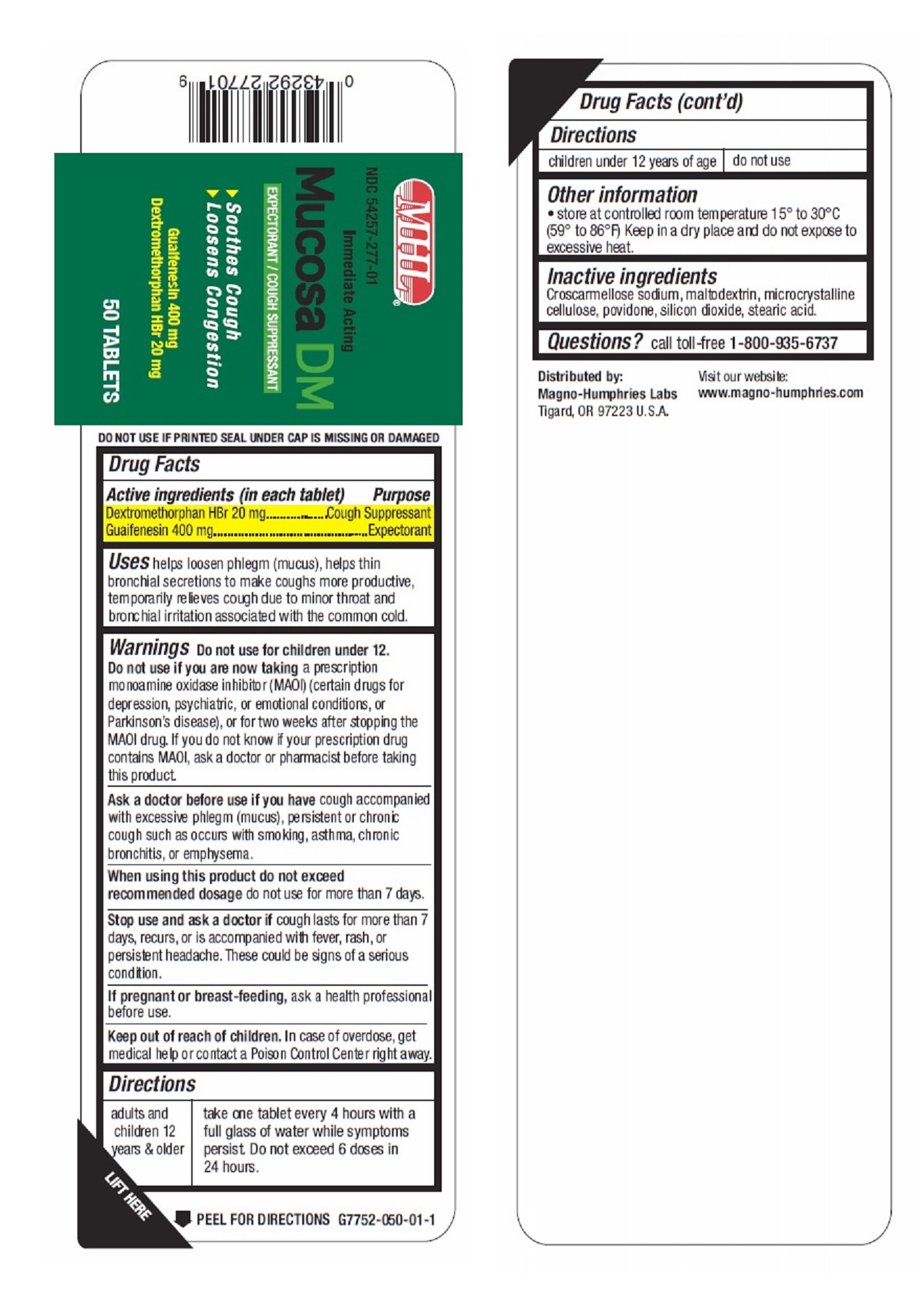 DRUG LABEL: Mucosa DM
NDC: 54257-277 | Form: TABLET
Manufacturer: Magno-Humphries, Inc.
Category: otc | Type: HUMAN OTC DRUG LABEL
Date: 20231027

ACTIVE INGREDIENTS: DEXTROMETHORPHAN HYDROBROMIDE 20 mg/1 1; GUAIFENESIN 400 mg/1 1
INACTIVE INGREDIENTS: CROSCARMELLOSE SODIUM; MALTODEXTRIN; MICROCRYSTALLINE CELLULOSE; POVIDONE, UNSPECIFIED; SILICON DIOXIDE; STEARIC ACID

Mucosa DM

MHL NDC 54257-277-01 immediate Acting

Mucosa DM

EXPECTORANT/COUGH SUPPRESSANT

Guaifenesin 400 mg

Dextromethorphan HBr 20 mg

50 TABLETS

- Soothes Cough
- Loosens Congestion

Active ingredients (in each tablet)

Dextromethorphan HBr 20mg

Guaifenesin 400 mg

Purpose

Dextromethorphan HBr 20mg.........Cough Suppressant Guaifenesin 400 mg.................................Expectorant

Uses

helps loosen phlegm (mucus), helps thin bronchial secretions to make coughs more productive, temporarily relieves cough due to minor throat and bronchial irritation associated with the common cold.

Warnings

a prescription monoamine oxidase inhibitor (MAOI) (certain drugs for depression, psychiatric, or emotional conditions, or Parkinson's disease), or for two weeks after stopping the MAOI drug. If you do not know if your prescription drug contains MAOI, ask a doctor or pharmacist before taking this product. Do not use for children under 12. Do not use if you are now taking

cougha ccompanied with excessive phlegm (mucus), persistent or chronic cough such as occurs with smoking, asthma, chronic bronchitis, or emphysema. Ask a doctor before use if you have

do not use for more than 7 days. When using this product do not exceed recommended dosage

cough lasts for more than 7 days, recurs, or is accompanied with fever, rash, or persistent headache. These could be signs of a serious condition. Stop use and ask a doctor if

ask a health professional before use. If pregnant or breast-feeding,

Keep out of reach of children.

In case of overdose, get medical help or contact a Poison Control Center right away.

Directions

adults and children 12 years & older - take one tablet every 4 hours with a full glass of water while symptoms persist. Do not exceed 6 doses in 24 hours.

children under 12 years of age - do not use

Other information

- store at controlled room temperature 15° to 30°C (59° to 86°F) Keep in a dry place and do not expose to excessive heat.

Inactive ingredients

Croscarmellose sodium, maltodextrin, microcrystalline cellulose, povidone, silicon dioxxide, stearic acid.

Questions?

call toll-free 1-800-935-6737

Distributed by: Magno-Humphries, Inc., OR 97223 U.S.A. Visit our website: www.magno-humphries.com

Tigard, OR 97223 U.S.A. Distributed by: Magno-Humphries, Inc.

Visit our website:
www.magno-humphries.com